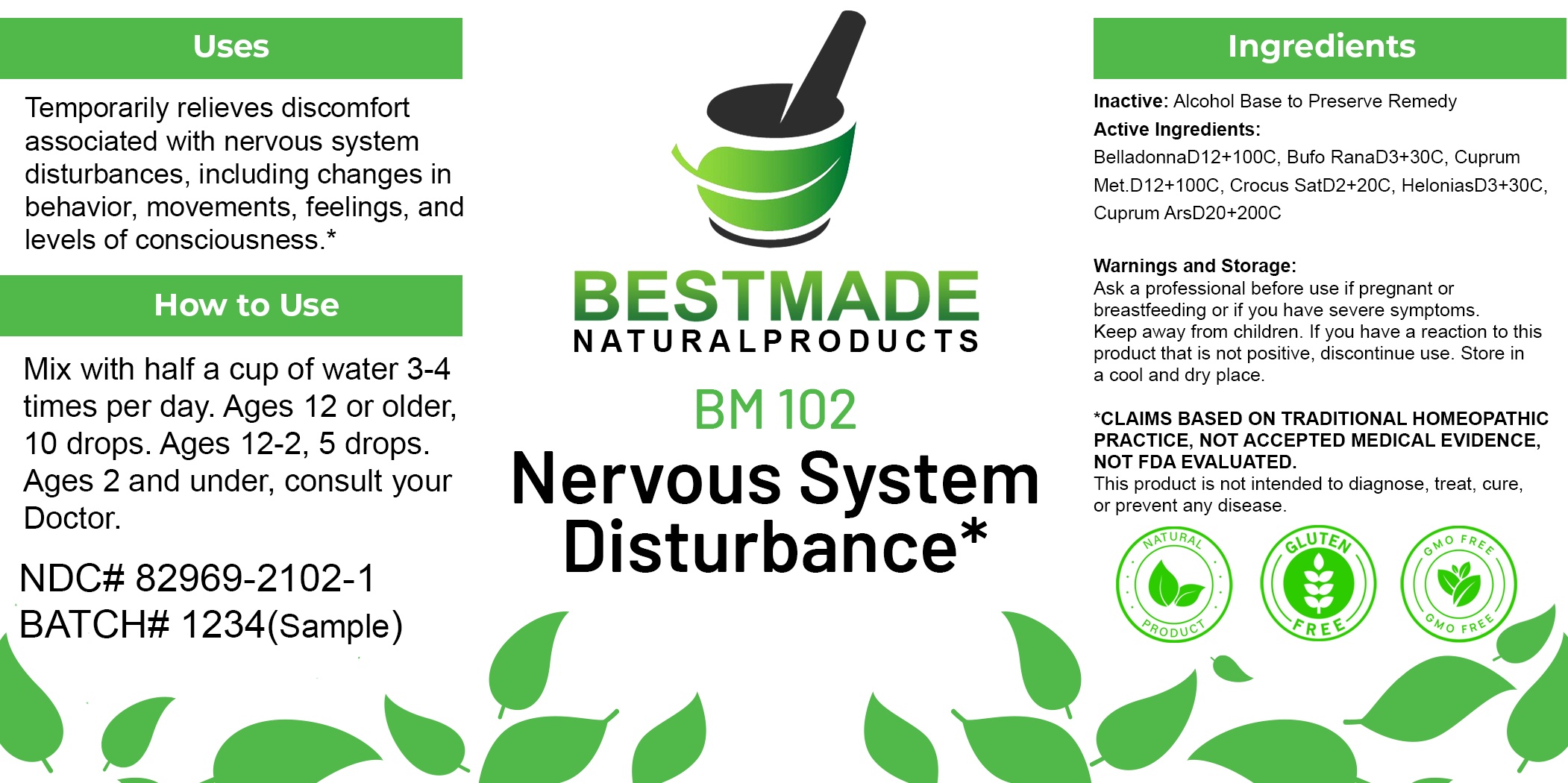 DRUG LABEL: Bestmade Natural Products BM102
NDC: 82969-2102 | Form: LIQUID
Manufacturer: Bestmade Natural Products
Category: homeopathic | Type: HUMAN OTC DRUG LABEL
Date: 20250207

ACTIVE INGREDIENTS: COPPER 30 [hp_C]/30 [hp_C]; BUFO BUFO CUTANEOUS GLAND 30 [hp_C]/30 [hp_C]; SAFFRON 30 [hp_C]/30 [hp_C]; CUPRIC ARSENITE 30 [hp_C]/30 [hp_C]; ATROPA BELLADONNA 30 [hp_C]/30 [hp_C]; CHAMAELIRIUM LUTEUM ROOT 30 [hp_C]/30 [hp_C]
INACTIVE INGREDIENTS: ALCOHOL 30 [hp_C]/30 [hp_C]

BM102

DOSAGE AND ADMINISTRATION

How to Use

Mix with half a cup of water 3-4 times per day. Ages 12 or older, 10 drops. Ages 12-2, 5 drops. Ages 2 and under, consult your Doctor.

INACTIVE INGREDIENT

Ingredients

Inactive: Alcohol Base to Preserve Remedy

ACTIVE INGREDIENT

Active Ingredients: Bufo Rana (Bufo Rana) D3+30C, Cuprum Met (Cuprum Metallicum) D12+100C, Morphind 100+100C, Crocus Sat (Crocus sativus or autumn crocus) D2+20C, Helonias (swamp pink) D3+30C, Cuprum Ars (Cuprum Arsenicosum) D20+200C

Uses

Temporarily relieves discomfort associated with nervous system disturbances, including changes in behavior, movements, feelings, and levels of consciousness.*

*CLAIMS BASED ON TRADITIONAL HOMEOPATHIC PRACTICE, NOT ACCEPTED MEDICAL EVIDENCE, NOT FDA EVALUATED.

This product is not intended to diagnose, treat, cure, or prevent any disease.

Uses

Temporarily relieves discomfort associated with nervous system disturbances, including changes in behavior, movements, feelings, and levels of consciousness.*

*CLAIMS BASED ON TRADITIONAL HOMEOPATHIC PRACTICE, NOT ACCEPTED MEDICAL EVIDENCE, NOT FDA EVALUATED.

This product is not intended to diagnose, treat, cure, or prevent any disease.

KEEP OUT OF REACH OF CHILDREN

Warnings and Storage:

Ask a professional before use if pregnant or breastfeeding or if you have severe symptoms. Keep away from children. If you have a reaction to this product that is not positive, discontinue use. Store in a cool and dry place.

Warnings and Storage:

Ask a professional before use if pregnant or breastfeeding or if you have severe symptoms. Keep away from children. If you have a reaction to this product that is not positive, discontinue use. Store in a cool and dry place.

*CLAIMS BASED ON TRADITIONAL HOMEOPATHIC PRACTICE, NOT ACCEPTED MEDICAL EVIDENCE, NOT FDA EVALUATED.

This product is not intended to diagnose, treat, cure, or prevent any disease.

Entire package label